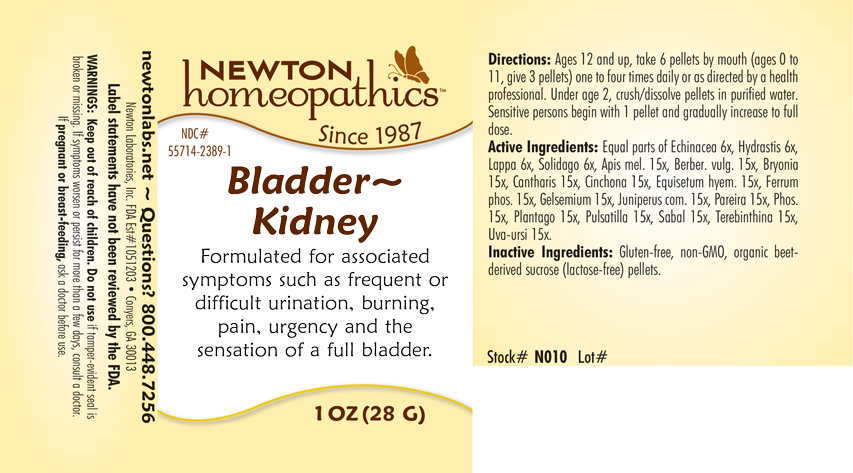 DRUG LABEL: Bladder - Kidney
NDC: 55714-2389 | Form: PELLET
Manufacturer: Newton Laboratories, Inc.
Category: homeopathic | Type: HUMAN OTC DRUG LABEL
Date: 20201124

ACTIVE INGREDIENTS: APIS MELLIFERA 15 [hp_X]/1 g; BERBERIS VULGARIS ROOT BARK 15 [hp_X]/1 g; BRYONIA ALBA ROOT 15 [hp_X]/1 g; LYTTA VESICATORIA 15 [hp_X]/1 g; CINCHONA OFFICINALIS BARK 15 [hp_X]/1 g; EQUISETUM HYEMALE 15 [hp_X]/1 g; FERROSOFERRIC PHOSPHATE 15 [hp_X]/1 g; GELSEMIUM SEMPERVIRENS ROOT 15 [hp_X]/1 g; JUNIPER BERRY 15 [hp_X]/1 g; CHONDRODENDRON TOMENTOSUM ROOT 15 [hp_X]/1 g; PHOSPHORUS 15 [hp_X]/1 g; PLANTAGO MAJOR 15 [hp_X]/1 g; PULSATILLA VULGARIS 15 [hp_X]/1 g; SAW PALMETTO 15 [hp_X]/1 g; TURPENTINE 15 [hp_X]/1 g; ARCTOSTAPHYLOS UVA-URSI LEAF 15 [hp_X]/1 g; ECHINACEA, UNSPECIFIED 6 [hp_X]/1 g; GOLDENSEAL 6 [hp_X]/1 g; ARCTIUM LAPPA ROOT 6 [hp_X]/1 g; SOLIDAGO VIRGAUREA FLOWERING TOP 6 [hp_X]/1 g
INACTIVE INGREDIENTS: SUCROSE

Bladder 2389P

OTC - KEEP OUT OF REACH OF CHILDREN SECTION

Keep out of reach of children.

OTC - PREGNANCY OR BREAST FEEDING SECTION

If pregnant or breast-feeding, ask a doctor before use.

WARNINGS SECTION

Warning: Keep out of reach of children. Do not use if tamper-evident seal is broken or missing. If symptoms persist for more than a few day, consult a doctor. If pregnant or breast-feeding, ask a doctor before use.

QUESTIONS SECTION

newtonlabs.net ~ Questions? 800.448.7256

Newton Laboratories, Inc. FDA Est # 1051203 - Conyers, GA 30013

INACTIVE INGREDIENT SECTION

Inactive Ingredients: Gluten-free, non-GMO, organic beet-derived sucrose (lactose free) pellets.

OTC - PURPOSE SECTION

Formulated for associated symptoms such as frequent or difficult urination, burning, pain, urgency and the sensation of a full bladder.

OTC - ACTIVE INGREDIENT SECTION

Equal parts of Echinacea 6x, Hydrastis 6x, Lappa 6x, Solidago 6x, Apis mel. 15x, Berber. vulg. 15x, Bryonia 15x, Cantharis 15x, Cinchona 15x, Equisetum hyem. 15x, Ferrum phos. 15x, Gelsemium 15x, Juniperus com. 15x, Pareira 15x, Phos. 15x, Plantago 15x, Pulsatilla 15x, Sabal 15x, Terebinthina 15x, Uva-ursi 15x.

DOSAGE & ADMINISTRATION SECTION

Directions: Ages 12 and up, take 6 pellets by mouth (ages 0 to 11, give 3 pellets) one to four times daily or as directed by a health professional. Under age 2, crush/dissolve pellets in purified water. Sensitive persons begin with 1 pellet and gradually increase to full dose.

INDICATIONS & USAGE SECTION

Bladder - Kidney Formulated for associated symptoms such as frequent or difficult urination, burning, pain, urgency and the sensation of a full bladder.